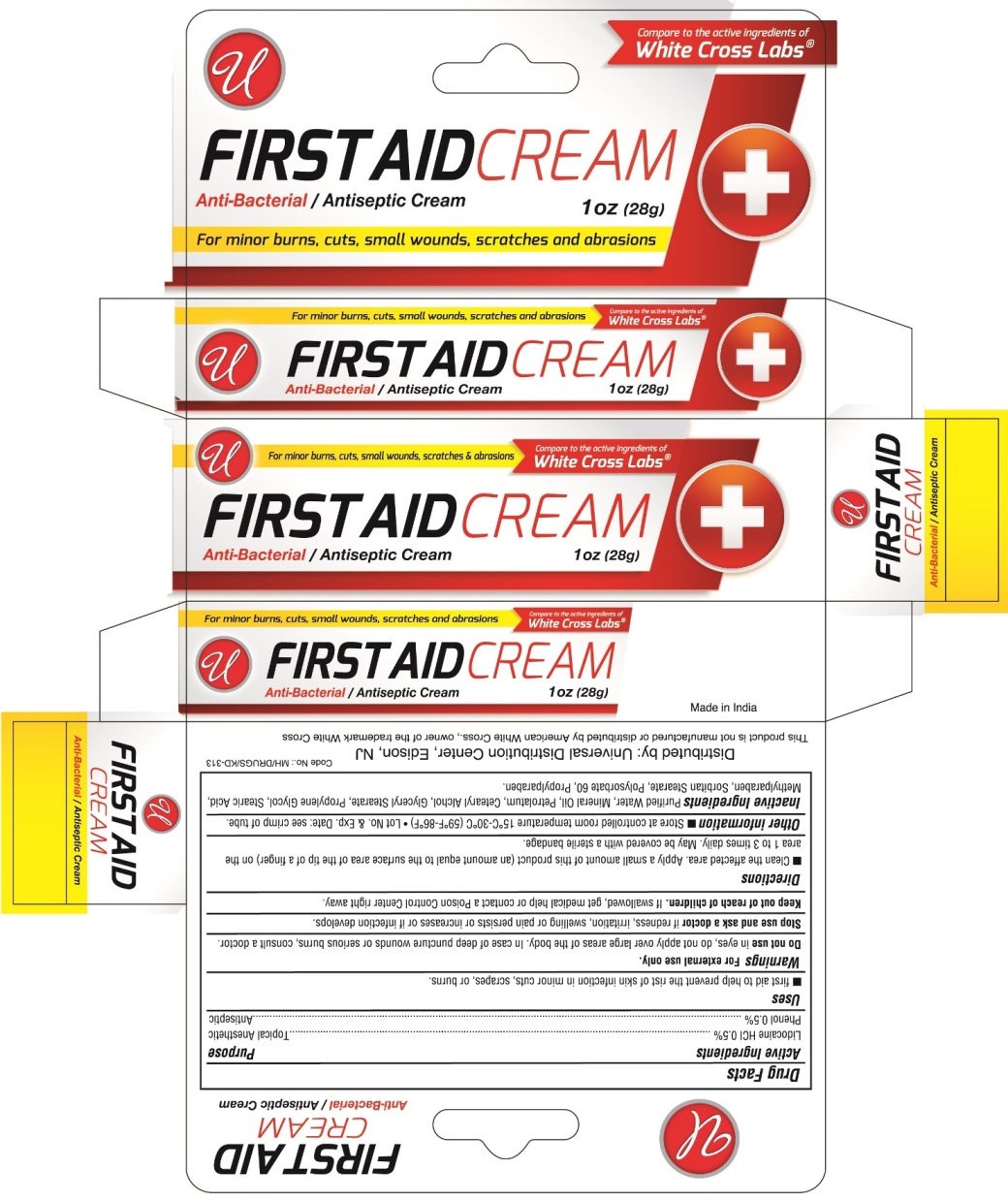 DRUG LABEL: First Aid
NDC: 52000-027 | Form: CREAM
Manufacturer: Universal Distribution Center LLC
Category: otc | Type: HUMAN OTC DRUG LABEL
Date: 20241018

ACTIVE INGREDIENTS: LIDOCAINE HYDROCHLORIDE 0.005 g/1 g; PHENOL 0.005 g/1 g
INACTIVE INGREDIENTS: WATER; MINERAL OIL; PETROLATUM; CETOSTEARYL ALCOHOL; GLYCERYL MONOSTEARATE; PROPYLENE GLYCOL; STEARIC ACID; METHYLPARABEN; SORBITAN MONOSTEARATE; POLYSORBATE 60; PROPYLPARABEN

First Aid Cream

Active Ingredients

Lidocaine HCl 0.5%

Phenol 0.5%

Purpose

Topical Anesthetic

Antiseptic

Uses

- first aid to help prevent the risk of skin infection in minor cuts, scrapes, or burns.

Warnings

For external use only

Do not use in eyes, do not apply over large areas of the body. In case of deep puncture wounds or serious burns, consult a doctor.

Stop use and ask a doctor if redness, irritation, swelling, or pain persists or increases or if infection develops.

Keep out of reach of children.

If swallowed, get medical help or contact a Poison Control Center right away.

Directions

- Clean the affected area. Apply a small amount of this product (an amount equal to the surface area of the tip of a finger) on the area 1 to 3 times daily. May be covered with sterile bandage.

Other Information

- Store at controlled room temperature 15ºC to 30ºC (59ºF to 86ºF).
- Lot No. & Exp. Date: see crimp of tube.

Inactive Ingredients

Purified Water, Mineral Oil, Petrolatum, Cetearyl Alcohol, Glyceryl Stearate, Propylene Glycol, Stearic Acid, Methylparaben, Sorbitan Stearate, Polysorbate 60, Propylparaben.

PACKAGE LABEL

PRINCIPAL DISPLAY PANEL

First Aid Cream
NET WT 1 OZ (28 g)